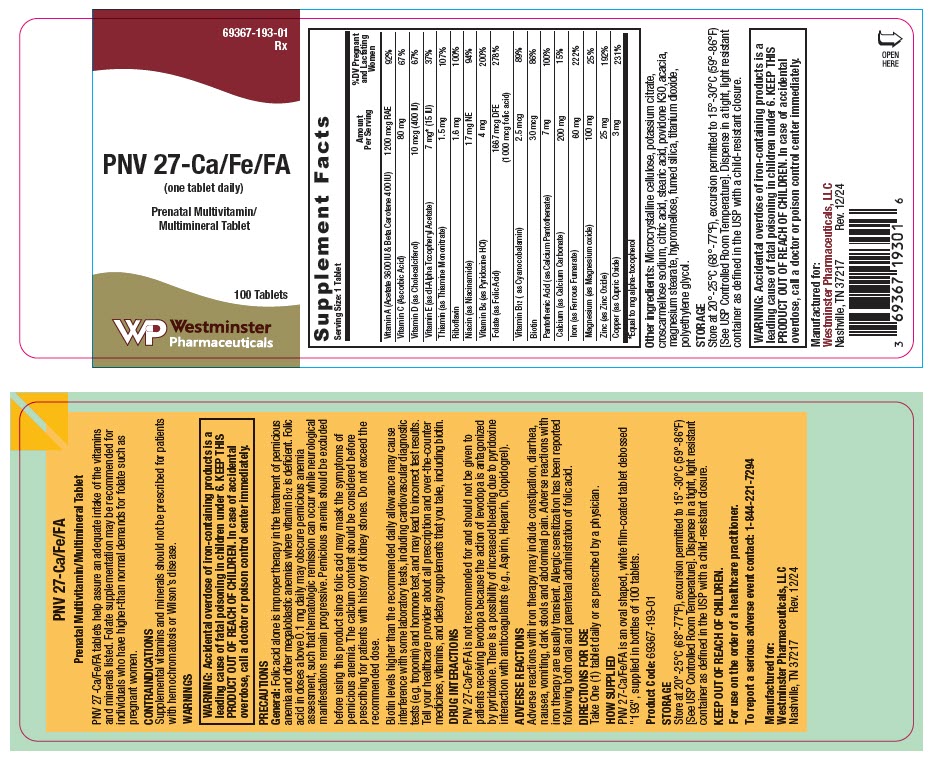 DRUG LABEL: PNV 27-Ca/Fe/FA
NDC: 69367-193 | Form: TABLET, FILM COATED
Manufacturer: Westminster Pharmaceuticals, LLC
Category: other | Type: DIETARY SUPPLEMENT
Date: 20250527

ACTIVE INGREDIENTS: VITAMIN A ACETATE 3600 [iU]/1 1; BETA CAROTENE 400 [iU]/1 1; ASCORBIC ACID 80 mg/1 1; CHOLECALCIFEROL 400 [iU]/1 1; .ALPHA.-TOCOPHEROL ACETATE, DL- 15 [iU]/1 1; THIAMINE MONONITRATE 1.5 mg/1 1; RIBOFLAVIN 1.6 mg/1 1; NIACINAMIDE 17 mg/1 1; PYRIDOXINE HYDROCHLORIDE 4 mg/1 1; FOLIC ACID 1 mg/1 1; CYANOCOBALAMIN 2.5 ug/1 1; BIOTIN 30 ug/1 1; CALCIUM PANTOTHENATE 7 mg/1 1; CALCIUM CARBONATE 200 mg/1 1; FERROUS FUMARATE 60 mg/1 1; MAGNESIUM OXIDE 100 mg/1 1; ZINC OXIDE 25 mg/1 1; CUPRIC OXIDE 3 mg/1 1
INACTIVE INGREDIENTS: MICROCRYSTALLINE CELLULOSE; POTASSIUM CITRATE ANHYDROUS; CROSCARMELLOSE SODIUM; CITRIC ACID MONOHYDRATE; STEARIC ACID; POVIDONE K30; ACACIA; MAGNESIUM STEARATE; HYPROMELLOSE, UNSPECIFIED; SILICON DIOXIDE; TITANIUM DIOXIDE; POLYETHYLENE GLYCOL, UNSPECIFIED

PNV 27-Ca/Fe/FA

HEALTH CLAIM

Prenatal Multivitamin/Multimineral Tablet

STATEMENT OF IDENTITY

Supplement Facts
Serving Size: 1 Tablet
 | Amount Per Serving | %DV Pregnant and Lactating Women
Vitamin A (Acetate 3600 IU & Beta Carotene 400 IU) | 1200 mcg RAE | 92%
Vitamin C (Ascorbic Acid) | 80 mg | 67%
Vitamin D (as Cholecalciferol) | 10 mcg (400 IU) | 67%
Vitamin E (as dl-Alpha Tocopheryl Acetate) | 7 mg [Equal to mg alpha-tocopherol] (15 IU) | 37%
Thiamin (as Thiamine Mononitrate) | 1.5 mg | 107%
Riboflavin | 1.6 mg | 100%
Niacin (as Niacinamide) | 17 mg NE | 94%
Vitamin B6 (as Pyridoxine HCl) | 4 mg | 200%
Folate (as Folic Acid) | 1667 mcg DFE (1000 mcg folic acid) | 278%
Vitamin B12 (as Cyanocobalamin) | 2.5 mcg | 89%
Biotin | 30 mcg | 86%
Pantothenic Acid (as Calcium Pantothenate) | 7 mg | 100%
Calcium (as Calcium Carbonate) | 200 mg | 15%
Iron (as Ferrous Fumarate) | 60 mg | 222%
Magnesium (as Magnesium oxide) | 100 mg | 25%
Zinc (as Zinc Oxide) | 25 mg | 192%
Copper (as Cupric Oxide) | 3 mg | 231%

Other ingredients: Microcrystalline cellulose, potassium citrate, croscarmellose sodium, citric acid, stearic acid, povidone K30, acacia, magnesium stearate, hypromellose, fumed silica, titanium dioxide, polyethylene glycol.

HEALTH CLAIM

PNV 27-Ca/Fe/FA tablets help assure an adequate intake of the vitamins and minerals listed. Folate supplementation may be recommended for individuals who have higher-than normal demands for folate such as pregnant women.

CONTRAINDICATIONS

Supplemental vitamins and minerals should not be prescribed for patients with hemochromatosis or Wilson's disease.

WARNINGS

WARNING: Accidental overdose of iron-containing products is a leading cause of fatal poisoning in children under 6. KEEP THIS PRODUCT OUT OF REACH OF CHILDREN. In case of accidental overdose, call a doctor or poison control center immediately.

PRECAUTIONS

General

Folic acid alone is improper therapy in the treatment of pernicious anemia and other megaloblastic anemias where vitamin B12 is deficient. Folic acid in doses above 0.1 mg daily may obscure pernicious anemia assessment, such that hematologic remission can occur while neurological manifestations remain progressive. Pernicious anemia should be excluded before using this product since folic acid may mask the symptoms of pernicious anemia. The calcium content should be considered before prescribing for patients with history of kidney stones. Do not exceed the recommended dose.

Biotin levels higher than the recommended daily allowance may cause interference with some laboratory tests, including cardiovascular diagnostic tests (e.g. troponin) and hormone test, and may lead to incorrect test results. Tell your healthcare provider about all prescription and over-the-counter medicines, vitamins, and dietary supplements that you take, including biotin.

DRUG INTERACTIONS

PNV 27-Ca/Fe/FA is not recommended for and should not be given to patients receiving levodopa because the action of levodopa is antagonized by pyridoxine. There is a possibility of increased bleeding due to pyridoxine interaction with anticoagulants (e.g., Aspirin, Heparin, Clopidogrel).

ADVERSE REACTIONS

Adverse reactions with iron therapy may include constipation, diarrhea, nausea, vomiting, dark stools and abdominal pain. Adverse reactions with iron therapy are usually transient. Allergic sensitization has been reported following both oral and parenteral administration of folic acid.

DIRECTIONS FOR USE

Take One (1) tablet daily or as prescribed by a physician.

HOW SUPPLIED

PNV 27-Ca/Fe/FA is an oval shaped, white film-coated tablet debossed "193", supplied in bottles of 100 tablets.

Product Code: 69367-193-01

STORAGE

Store at 20°-25°C (68°-77°F), excursion permitted to 15°-30°C (59°-86°F) [See USP Controlled Room Temperature]. Dispense in a tight, light resistant container as defined in the USP with a child-resistant closure.

KEEP OUT OF REACH OF CHILDREN.

For use on the order of a healthcare practitioner.

To report a serious adverse event contact: 1-844-221-7294

HEALTH CLAIM

Manufactured for:
Westminster Pharmaceuticals, LLC
Nashville, TN 37217

Rev. 12/24

PRINCIPAL DISPLAY PANEL - 100 Tablet Bottle Label

69367-193-01
Rx

PNV 27-Ca/Fe/FA
(one tablet daily)

Prenatal Multivitamin/
Multimineral Tablet

100 Tablets

Westminster
Pharmaceuticals